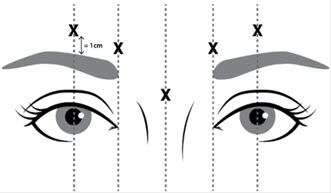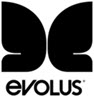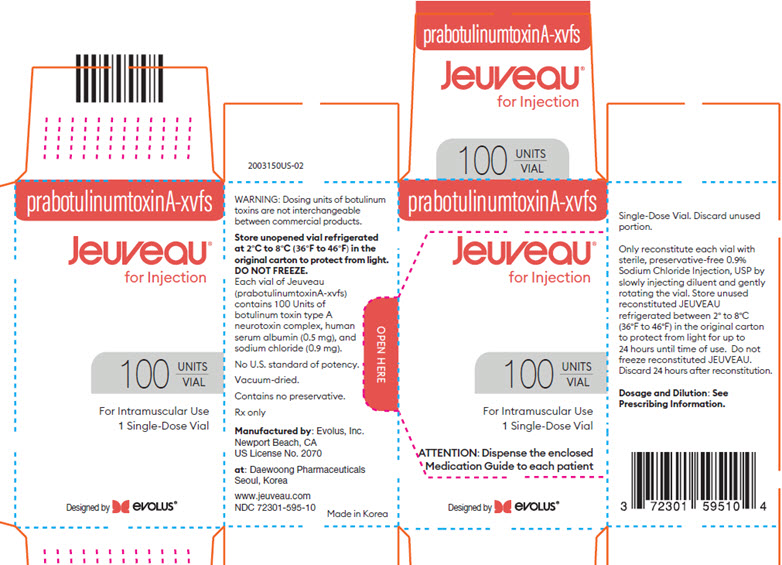 DRUG LABEL: Jeuveau
NDC: 72301-595 | Form: POWDER
Manufacturer: Evolus, Inc.
Category: prescription | Type: HUMAN PRESCRIPTION DRUG LABEL
Date: 20230428

ACTIVE INGREDIENTS: BOTULINUM TOXIN TYPE A 100 [USP'U]/1 1
INACTIVE INGREDIENTS: ALBUMIN HUMAN; SODIUM CHLORIDE

HIGHLIGHTS OF PRESCRIBING INFORMATION

These highlights do not include all the information needed to use JEUVEAU® safely and effectively. See full prescribing information for JEUVEAU.
JEUVEAU (prabotulinumtoxinA-xvfs) for injection, for intramuscular use
Initial U.S. Approval: 2019

WARNING: DISTANT SPREAD OF TOXIN EFFECT

See full prescribing information for complete boxed warning.

The effects of all botulinum toxin products, including JEUVEAU, may spread from the area of injection to produce symptoms consistent with botulinum toxin effects. These symptoms have been reported hours to weeks after injection. Swallowing and breathing difficulties can be life threatening and there have been reports of death. JEUVEAU is not approved for the treatment of spasticity or any conditions other than glabellar lines. (5.1)

1 INDICATIONS AND USAGE

JEUVEAU is an acetylcholine release inhibitor and a neuromuscular blocking agent indicated for the temporary improvement in the appearance of moderate to severe glabellar lines associated with corrugator and/or procerus muscle activity in adult patients (1)

2 DOSAGE AND ADMINISTRATION

Glabellar Lines Administration: 0.1 mL (4 Units) by intramuscular injection into each of five sites, for a total dose of 20 Units (2.2, 2.3)

3 DOSAGE FORMS AND STRENGTHS

For Injection: 100 Units vacuum-dried powder in a single-dose vial (3)

4 CONTRAINDICATIONS

- Hypersensitivity to any botulinum toxin preparation or to any of the components in the formulation (4.1)
- Infection at the injection site (4.2)

5 WARNINGS AND PRECAUTIONS

- Potency Units of JEUVEAU are not interchangeable with other preparations of botulinum toxin products (5.2, 11)
- Spread of toxin effects; swallowing and breathing difficulties can lead to death. Seek immediate medical attention if respiratory, speech, or swallowing difficulties occur (5.2, 5.7)
- Potential serious adverse reactions after JEUVEAU injections for unapproved uses (5.3)
- Adverse event reports have been received involving the cardiovascular system, some with fatal outcomes. Use caution when administering to patients with pre-existing cardiovascular disease (5.5)
- Concomitant neuromuscular disorder may exacerbate clinical effects of treatment (5.6)
- Use with caution in patients with compromised respiratory function or dysphagia (5.7)

6 ADVERSE REACTIONS

The most common adverse reactions are headache (12%), eyelid ptosis (2%), upper respiratory tract infection (3%), and increased white blood cell count (1%) (6.1)

To report SUSPECTED ADVERSE REACTIONS, contact Evolus at [1-877-386-5871] or FDA at 1-800-FDA-1088 or www.fda.gov/medwatch.

7 DRUG INTERACTIONS

Closely observe patients receiving concomitant treatment of JEUVEAU and aminoglycosides or other agents interfering with neuromuscular transmission (e.g., curare-like agents), or muscle relaxants because JEUVEAU’s effect may be potentiated (7)

FULL PRESCRIBING INFORMATION

WARNING: DISTANT SPREAD OF TOXIN EFFECT

The effects of all botulinum toxin products, including JEUVEAU, may spread from the area of injection to produce symptoms consistent with botulinum toxin effects. These symptoms have been reported hours to weeks after injection. Swallowing and breathing difficulties can be life threatening and there have been reports of death. JEUVEAU is not approved for the treatment of spasticity or any conditions other than glabellar lines. [See Warnings and Precautions (5.1)]

1 INDICATIONS AND USAGE

JEUVEAU is indicated for the temporary improvement in the appearance of moderate to severe glabellar lines associated with corrugator and/or procerus muscle activity in adult patients.

2 DOSAGE AND ADMINISTRATION

2.1 Instructions for Safe Use

The potency Units of JEUVEAU (prabotulinumtoxinA-xvfs) for injection are specific to the preparation and assay method utilized. They are not interchangeable with other preparations of botulinum toxin products and, therefore, units of biological activity of JEUVEAU cannot be compared to nor converted into units of any other botulinum toxin products assessed with any other specific assay method [see Warnings and Precautions (5.2) and Description (11)].

Retreatment of JEUVEAU should be administered no more frequently than every three months. Consideration of the cumulative dose is necessary when treating adult patients with JEUVEAU for glabellar lines if other botulinum toxin products are or have been used to treat other indications approved for those products.

The safe and effective use of JEUVEAU depends upon proper storage of the product, selection of the correct dose, and proper reconstitution and administration techniques. Physicians administering JEUVEAU must understand the relevant neuromuscular and/or orbital anatomy of the area involved and any alterations to the anatomy due to prior surgical procedures [see Warnings and Precautions (5.4)].

2.2 Preparation and Dilution Technique

JEUVEAU is supplied in a single-dose 100 Unit vial. Prior to intramuscular injection, reconstitute each vacuum-dried vial of JEUVEAU with only sterile, preservative-free 0.9% Sodium Chloride Injection, USP to obtain a reconstituted solution at a concentration of 4 Units/0.1 mL and a total treatment dose of 20 Units in 0.5 mL (see Table 1). Slowly inject the diluent into the vial. Discard the vial if a vacuum does not pull the diluent into the vial. Dispose of any unused saline. Gently mix JEUVEAU with 0.9% Sodium Chloride Injection USP by rotating the vial. JEUVEAU should be administered within 24 hours after reconstitution. During this time period, unused reconstituted JEUVEAU should be stored in a refrigerator between 2° to 8°C (36°F to 46°F) in the original carton to protect from light for up to 24 hours until time of use. Do not freeze reconstituted JEUVEAU. JEUVEAU vials are for single-dose only. After reconstitution, JEUVEAU should be used for only one injection session and for only one patient. Discard any remaining solution after administration.

Table 1. Dilution Instructions for JEUVEAU Vials (100 Units)
Diluent [Preservative-free 0.9% Sodium Chloride Injection, USP] Added to 100 Unit Vial | Resulting Dose Units per 0.1 mL
2.5 mL | 4 Units

Reconstituted JEUVEAU should be clear, colorless, and free of particulate matter otherwise it should not be injected. Parenteral drug products should be inspected visually for particulate matter and discoloration prior to administration.

2.3 Administration

Glabellar facial lines arise from the activity of the corrugator and orbicularis oculi muscles. These muscles move the brow medially and the procerus and depressor supercilii pull the brow inferiorly. This creates a frown or “furrowed brow”. The location, size, and use of the muscles vary markedly among individuals. Lines induced by facial expression occur perpendicular to the direction of action of contracting facial muscles. An effective dose for facial lines is determined by gross observation of the patient’s ability to activate the superficial muscles injected.

In order to reduce the complication of eyelid ptosis the following steps should be taken:

- Avoid injection near the levator palpebrae superioris, particularly in patients with larger brow depressor complexes.
- Lateral corrugator injections should be placed at least 1 cm above the bony supraorbital ridge.
- Ensure the injected volume/dose is accurate and where feasible kept to a minimum.
- Avoid injecting JEUVEAU closer than 1 centimeter above the central eyebrow.

Draw at least 0.5 mL of the properly reconstituted JEUVEAU into a sterile syringe and expel any air bubbles in the syringe barrel. Remove the needle used to reconstitute the product and attach a 30-33 gauge needle. Confirm the patency of the needle. Inject a dose of 0.1 mL (4 Units) intramuscularly into each of five sites: the inferomedial and superior middle of each corrugator, and one in the mid-line of the procerus muscle for a total dose of 20 Units (See Figure 1).

Figure 1

3 DOSAGE FORMS AND STRENGTHS

- For injection: 100 Units, vacuum-dried powder in a single-dose vial for reconstitution with preservative-free 0.9% Sodium Chloride Injection, USP.

4 CONTRAINDICATIONS

4.1 Known Hypersensitivity to Botulinum Toxin

JEUVEAU is contraindicated in individuals with known hypersensitivity to any botulinum toxin preparation or to any of the components in the formulation [See Warnings and Precautions (5.4)].

4.2 Infection at the Injection Site(s)

JEUVEAU is contraindicated in the presence of infection at the proposed injection site(s).

5 WARNINGS AND PRECAUTIONS

5.1 Spread of Toxin Effect

Postmarketing safety data from other approved botulinum toxins suggest that botulinum toxin effects may be observed beyond the site of local injection. The symptoms are consistent with the mechanism of action of botulinum toxin and may include asthenia, generalized muscle weakness, diplopia, ptosis, dysphagia, dysphonia, dysarthria, urinary incontinence, blurred vision, and breathing difficulties. These symptoms have been reported hours to weeks after injection. Swallowing and breathing difficulties can be life threatening and there have been reports of death related to spread of toxin effects. In unapproved uses, including upper limb spasticity in children and approved indications, symptoms consistent with spread of toxin effect have been reported at doses comparable to or lower than the maximum recommended total dose [see Use in Specific Populations (8.4)]. JEUVEAU is not approved for the treatment of spasticity or any conditions other than glabellar lines. Patients or caregivers should be advised to seek immediate medical care if swallowing, speech, or respiratory difficulties occur.

5.2 Lack of Interchangeability between Botulinum Toxin Products

The potency Units of JEUVEAU are specific to the preparation and assay method utilized. They are not interchangeable with other preparations of botulinum toxin products and, therefore, units of biological activity of JEUVEAU cannot be compared to nor converted into units of any other botulinum toxin products assessed with any other specific assay method [see Description (11)].

5.3 Serious Adverse Reactions with Unapproved Use

Serious adverse reactions, including excessive weakness, dysphagia, and aspiration pneumonia, with some adverse reactions associated with fatal outcomes, have been reported in patients who received botulinum toxin injections for unapproved uses. In these cases, the adverse reactions were not necessarily related to distant spread of toxin, but may have resulted from the administration of botulinum toxin products to the site of injection and/or adjacent structures. In several of the cases, patients had pre-existing dysphagia or other significant disabilities. There is insufficient information to identify factors associated with an increased risk for adverse reactions associated with the unapproved uses of botulinum toxin products.

5.4 Hypersensitivity Reactions

Serious and/or immediate hypersensitivity reactions have been reported for botulinum toxin products. These reactions include anaphylaxis, serum sickness, urticaria, soft tissue edema, and dyspnea. If such a reaction occurs, further injection of JEUVEAU should be discontinued and appropriate medical therapy immediately instituted. The use of JEUVEAU in patients with a known hypersensitivity to any botulinum neurotoxin or to any of the components in the formulation could lead to a life threatening allergic reaction [See Contraindications (4.1)].

5.5 Cardiovascular System

There have been reports following administration of botulinum toxins of adverse events involving the cardiovascular system, including arrhythmia and myocardial infarction, some with fatal outcomes. Some of these patients had risk factors including pre-existing cardiovascular disease. Use caution when administering to patients with pre-existing cardiovascular disease.

5.6 Increased Risk of Clinically Significant Effects with Pre-Existing Neuromuscular Disorders

Individuals with peripheral motor neuropathic diseases, amyotrophic lateral sclerosis, or neuromuscular junction disorders (e.g., myasthenia gravis or Lambert-Eaton syndrome) were excluded from the clinical studies of JEUVEAU. Patients with neuromuscular disorders may be at increased risk of clinically significant effects including generalized muscle weakness, diplopia, ptosis, dysphonia, dysarthria, severe dysphagia, and respiratory compromise from typical doses of JEUVEAU.

5.7 Dysphagia and Breathing Difficulties

Treatment with botulinum toxin products, including JEUVEAU, can result in swallowing or breathing difficulties. Patients with preexisting swallowing or breathing difficulties may be more susceptible to these complications. In most cases, this has been a consequence of weakening of muscles in the area of injection that are involved in breathing or oropharyngeal muscles that control swallowing or breathing [see Warnings and Precautions (5.1)].

Deaths as a complication of severe dysphagia have been reported after treatment with botulinum toxin. Dysphagia may persist for several months, and require use of a feeding tube to maintain adequate nutrition and hydration. Aspiration may result from severe dysphagia and is a particular risk when treating patients in whom swallowing or respiratory function is already compromised.

Treatment with botulinum toxins, including JEUVEAU, may weaken neck muscles that serve as accessory muscles of ventilation. This may result in a critical loss of breathing capacity in patients with respiratory disorders who may have become dependent upon these accessory muscles. There have been postmarketing reports from other botulinum toxin products of serious breathing difficulties, including respiratory failure.

Patients with smaller neck muscle mass and patients who require bilateral injections into the sternocleidomastoid muscle for the treatment of cervical dystonia have been reported to be at greater risk for dysphagia. Injections into the levator scapulae for the treatment cervical dystonia may be associated with an increased risk of upper respiratory infection and dysphagia. JEUVEAU is not approved for the treatment of cervical dystonia.

Patients treated with botulinum toxin products, including JEUVEAU, may require immediate medical attention should they develop problems with swallowing, speech, or breathing. These reactions can occur within hours to weeks after injection with botulinum toxin [see Warnings and Precautions (5.1)].

5.8 Pre-existing Conditions at the Injection Site

Caution should be used when JEUVEAU treatment is used in the presence of inflammation at the proposed injection site(s) or when excessive weakness or atrophy is present in the target muscle(s).

Caution should be used when JEUVEAU treatment is used in patients who have marked facial asymmetry, ptosis, excessive dermatochalasis, deep dermal scarring, thick sebaceous skin, or when subjects do not respond to 20 Units of botulinum toxin (e.g., the inability to substantially lessen glabellar lines even by physically spreading them apart). Do not exceed the recommended dosage and frequency of administration of JEUVEAU.

5.9 Ophthalmic Adverse Reactions in Patients Treated with Botulinum Toxin Products

Dry eye has been reported with the use of botulinum toxin products in the treatment of glabellar lines. Reduced tear production, reduced blinking, and corneal disorders may occur with use of botulinum toxins, including JEUVEAU. If symptoms of dry eye (e.g., eye irritation, photophobia, or visual changes) persist, consider referring patients to an ophthalmologist [see Warnings and Precautions (5.1)].

5.10 Human Albumin and Transmission of Viral Diseases

This product contains albumin, a derivative of human blood. Based on effective donor screening and product manufacturing processes, it carries an extremely remote risk for transmission of viral diseases and variant Creutzfeldt-Jakob disease (vCJD). There is a theoretical risk for transmission of Creutzfeldt-Jakob disease (CJD), but if that risk actually exists, the risk of transmission would also be considered extremely remote. No cases of transmission of viral diseases, CJD, or vCJD have ever been identified for licensed albumin or albumin contained in other licensed products.

6 ADVERSE REACTIONS

The following serious adverse reactions are discussed in greater detail in other sections of the labeling:

- Spread of Toxin Effects [see Warnings and Precautions (5.1)]
- Hypersensitivity [see Contraindications (4.1) and Warnings and Precautions (5.4)]
- Dysphagia and Breathing Difficulties [See Warnings and Precautions (5.7)]

6.1 Clinical Trials Experience

Because clinical trials are conducted under widely varying conditions, the adverse reaction rates observed in the clinical trials of a drug cannot be directly compared to rates in the clinical trials of another drug and may not reflect the rates observed in clinical practice.

In general, most adverse reactions occur within the first week following injection of JEUVEAU and while generally transient, may have a duration of several months or longer. Localized pain, infection, inflammation, tenderness, swelling, erythema, and/or bleeding/bruising may be associated with the injection. Needle-related pain and/or anxiety may result in vasovagal responses, including syncope and hypotension, which may require appropriate medical therapy.

Local weakness of the injected muscle(s) represents the expected pharmacological action of botulinum toxin. However, weakness of nearby muscles may also occur due to spread of toxin effect [see Warnings and Precautions (5.1)].

Glabellar Lines

The adverse reactions below reflect exposure to JEUVEAU in the treatment of glabellar lines in placebo-controlled trials [See Clinical Studies (14)].

Table 2. Adverse Reactions Reported at Higher Frequency (≥1%) in the JEUVEAU Group Compared to the Placebo Group
 | JEUVEAU EV-001, EV-002 N=492 n (%) | PLACEBO EV-001, EV-002, N=162 n (%)
Headache | 57 (12%) | 21 (13%)
Eyelid Ptosis | 8 (2%) | 0 (0%)
Upper Respiratory Tract Infection | 13 (3%) | 1 (1%)
White blood cell count increase | 6 (1%) | 0 (0%)

Two multi-center, open label, 1-year repeat dose safety trials, EV-004 [NCT02184988] and EV-006 [NCT02428608], were also conducted with JEUVEAU. Both trials evaluated repeat treatments of 20 units of JEUVEAU, up to a maximum total of 80 units, for the treatment of moderate to severe glabellar lines in adult subjects. Of the 922 subjects enrolled, the median number of treatments was three. The adverse events profile was similar to that reported in single dose trials.

6.2 Immunogenicity

As with all therapeutic proteins, there is a potential for immunogenicity. The detection of antibody formation is highly dependent on the sensitivity and specificity of the assay. Additionally, the observed incidence of antibody (including neutralizing antibody) positivity in an assay may be influenced by several factors including assay methodology, sample handling, timing of sample collection, concomitant medications, and underlying disease. For these reasons, comparison of the incidence of antibodies to prabotulinumtoxinA-xvfs in the studies described below, with the incidence of antibodies in other studies, or to other products may be misleading.

Treatment with botulinum toxins may result in the formation of antibodies that may reduce the effectiveness of subsequent treatments by inactivating biological activity of the toxin. Among 1,414 subjects treated with prabotulinumtoxinA-xvfs, 2 subjects were found to have pre-existing antibodies and 2 subjects had treatment-emergent antibodies.

7 DRUG INTERACTIONS

No formal drug interaction studies have been conducted with JEUVEAU (prabotulinumtoxinA-xvfs) for injection. However, the potential for certain drugs to potentiate the effects of JEUVEAU warrant consideration given the potential risks involved and should be used with caution.

- Aminoglycosides or other agents interfering with neuromuscular transmission
- Anticholinergic drugs
- Botulinum neurotoxin products
- Muscle relaxant

8 USE IN SPECIFIC POPULATIONS

8.1 Pregnancy

Risk Summary

The limited available data on JEUVEAU use in pregnant women are insufficient to inform a drug associated risk of adverse developmental outcomes. An embryofetal developmental study conducted with JEUVEAU in pregnant rats revealed no treatment-related effects to the developing fetus when JEUVEAU was administered intramuscularly during organogenesis at doses up to 12 times the maximum recommended human dose (MRHD) (see Data).

The estimated background risk of major birth defects and miscarriage for the indicated population is unknown. All pregnancies have a background risk of birth defect, loss, or other adverse outcomes. In the U.S. general population, the estimated background risk of major birth defects and miscarriage in clinically recognized pregnancies is 2% to 4% and 15% to 20%, respectively.

Data

Animal Data

In an embryofetal developmental study, intramuscular doses up to 4 Unit/kg JEUVEAU were administered to pregnant rats once daily during organogenesis (gestation days 6 to 16). No maternal or embryofetal toxicities were observed at doses up to 4 Unit/kg (12 times the MRHD of 20 Units, based on Unit/kg comparison).

8.2 Lactation

There is no information regarding the presence of prabotulinumtoxinA-xvfs in human or animal milk, its effects on the breastfed infant, or on milk production.

The developmental and health benefits of breastfeeding should be considered along with the mother’s clinical need for JEUVEAU and any potential adverse effects on the breastfed infant from JEUVEAU or from the underlying maternal condition

8.4 Pediatric Use

Safety and effectiveness in pediatric patients have not been established.

8.5 Geriatric Use

The two clinical trials of JEUVEAU included 68 subjects age 65 and greater. Although no differences in safety or efficacy were observed between older and younger subjects, clinical studies of JEUVEAU did not include sufficient numbers of subjects aged 65 and over to determine whether they respond differently from younger subjects.

10 OVERDOSAGE

There is no information regarding overdose from clinical studies of JEUVEAU. Excessive doses of JEUVEAU (prabotulinumtoxinA-xvfs) injection may be expected to produce neuromuscular weakness with a variety of symptoms.

Symptoms of overdose are likely not to be present immediately following injection. Should accidental injection or oral ingestion occur, or overdose be suspected, these patients should be considered for further medical evaluation and appropriate medical therapy immediately instituted, which may include hospitalization. The person should be medically supervised for several weeks for signs and symptoms of systemic muscular weakness which could be local or distant from the site of injection [see Boxed Warning and Warnings and Precautions (5.1)].

If the musculature of the oropharynx and esophagus are affected, aspiration may occur which may lead to development of aspiration pneumonia. If the respiratory muscles become paralyzed or sufficiently weakened, intubation and assisted respiration may be necessary until recovery takes place. Supportive care could involve the need for a tracheostomy and/or prolonged mechanical ventilation, in addition to other general supportive care.

In the event of overdose, antitoxin raised against botulinum toxin is available from the Centers for Disease Control and Prevention (CDC) in Atlanta, GA. However, the antitoxin will not reverse any botulinum toxin-induced effects already apparent by the time of antitoxin administration. In the event of suspected or actual cases of botulinum toxin poisoning, please contact your local or state Health Department to process a request for antitoxin through the CDC. If you do not receive a response within 30 minutes, please contact the CDC directly at 1-770-488-7100. More information can be obtained at http://www.cdc.gov/ncidod/srp/drugs/formulary.html#1a.

11 DESCRIPTION

PrabotulinumtoxinA-xvfs is an acetylcholine release inhibitor and a neuromuscular blocking agent. PrabotulinumtoxinA-xvfs is supplied as a sterile, vacuum-dried powder in a single-dose vial intended for intramuscular use after reconstitution. PrabotulinumtoxinA-xvfs is a 900 kDa botulinum toxin type A, produced from fermentation of Clostridium botulinum.

The primary release procedure for JEUVEAU uses an animal based potency assay to determine the potency relative to a reference standard. The assay is specific to Evolus’ product, JEUVEAU. One Unit of JEUVEAU corresponds to the calculated median intraperitoneal lethal dose (LD50) in mice. Due to specific details of this assay, Units of biological activity of JEUVEAU cannot be converted into Units of any other botulinum toxin or any toxin assessed with any other specific assay method.

Each vial of JEUVEAU (prabotulinumtoxinA-xvfs) for injection contains 100 Units of botulinum toxin type A neurotoxin complex, human serum albumin (0.5 mg), and sodium chloride (0.9 mg) in a sterile, vacuum-dried form without a preservative.

12 CLINICAL PHARMACOLOGY

12.1 Mechanism of Action

JEUVEAU blocks neuromuscular transmission by binding to acceptor sites on motor nerve terminals, entering the nerve terminals, and inhibiting the release of acetylcholine. This inhibition occurs as the neurotoxin cleaves SNAP-25, a protein integral to the successful docking and release of acetylcholine from vesicles situated within nerve endings. When injected intramuscularly at therapeutic doses, JEUVEAU produces partial chemical denervation of the muscle resulting in a localized reduction in muscle activity. In addition, the muscle may atrophy, axonal sprouting may occur, and extrajunctional acetylcholine receptors may develop. There is evidence that reinnervation of the muscle may occur, thus slowly reversing muscle denervation produced by JEUVEAU.

12.2 Pharmacodynamics

No formal pharmacodynamic studies have been conducted with JEUVEAU.

12.3 Pharmacokinetics

Using currently available analytical technology, it is not possible to detect JEUVEAU in the peripheral blood following intramuscular injection at the recommended doses.

No drug interaction studies have been conducted with JEUVEAU.

13 NONCLINICAL TOXICOLOGY

13.1 Carcinogenesis, Mutagenesis, Impairment of Fertility

Animal studies have not been conducted to evaluate the carcinogenic, mutagenic, or impairment of fertility potential of JEUVEAU.

14 CLINICAL STUDIES

Two randomized, multi-center, double-blind, placebo-controlled trials (EV-001 [NCT02334423] and EV-002 [NCT02334436]) of identical design were conducted to evaluate JEUVEAU for use in the temporary improvement of the appearance of moderate to severe glabellar facial lines. These trials enrolled 654 subjects, randomized 3 to 1 to a single treatment with JEUVEAU (n=492) or placebo (n=162).

The trials enrolled healthy adults (ranging in age from 18 to 81) with glabellar lines of at least moderate severity at maximum frown. The trials excluded subjects who had ptosis, deep dermal scarring, or an inability to substantially lessen glabellar lines even by physically spreading the glabellar lines apart. Injection volume was 0.1 mL/injection site, for a dose/injection site in the active treatment groups of 4 Units. Subjects were injected intramuscularly at five sites, one in the procerus muscle and two in each corrugator supercilii muscle, for a total dose in the active treatment groups of 20 Units.

The primary efficacy endpoint was measured at Day 30 and was defined as the proportion of subjects achieving ≥2-grade improvement from baseline at maximum frown, as assessed independently by both the investigator and the subject using the Glabellar Line Scale (GLS). The GLS is a 4-point grading scale (0=none, 1=mild, 2= moderate, 3=severe). The results of these two efficacy trials are presented below (See Table 3).

The mean age was 51 years, with 68 subjects (10%) ≥ 65 years of age. Most of the subjects were women (91%), and a majority of the subjects were white (84%).

Table 3. Trials EV-001 and EV-002: Composite Investigator and Subject Assessment of Glabellar Line Severity at Maximum Frown at Day 30 – Responder Rates (% of Subjects Achieving ≥ 2-Grade Improvement from Baseline)
Trial | JEUVEAU | Placebo
Trial EV-001 | N=246; 68% | N=84; 1%
Trial EV-002 | N=246; 70% | N=78; 1%

16 HOW SUPPLIED/STORAGE AND HANDLING

JEUVEAU (prabotulinumtoxinA-xvfs) for injection is a vacuum-dried powder supplied in a single-dose vial in the following size:

100 Units (NDC 72301-595-10)

Storage

Unopened vials of JEUVEAU should be stored in a refrigerator between 2° to 8°C (36° to 46° F) in the original carton to protect from light.

17 PATIENT COUNSELING INFORMATION

Advise the patient to read the FDA-approved patient labeling (Medication Guide).

Advise patients to inform their doctor if they develop any unusual symptoms (including difficulty with swallowing, speaking, or breathing), or if any known symptom persists or worsens [see Warnings and Precautions (5.1, 5.4)].

Inform patients that JEUVEAU injection may cause eye dryness. Advise patients to report symptoms of eye dryness (e.g., eye pain, eye irritation, photosensitivity, or changes in vision) to their doctor [see Warnings and Precautions (5.9)].

Inform patients that if loss of strength, muscle weakness, blurred vision, or drooping eyelids occur, they should avoid driving a car or engaging in other potentially hazardous activities.

Manufactured by: Evolus Inc.
520 Newport Center Drive, Suite 1200, Newport Beach, CA 92660

U.S. License Number 2070

at: Daewoong Pharmaceutical Co., Ltd.
12, Bongeunsa-ro 114-gil, Gangnam-gu,
Seoul, 06170 Korea

©2023 Evolus. All rights reserved.

All Trademarks are the property of their respective owners.

DWG-131 Rev. E

MEDICATION GUIDE

JEUVEAU (pronounced Jū vō)

(prabotulinumtoxinA-xvfs)

for Injection

What is the most important information I should know about JEUVEAU?

JEUVEAU may cause serious side effects that can be life threatening. Call your healthcare provider or get medical help right away if you have any of these problems after treatment with JEUVEAU:

- Problems swallowing, speaking, or breathing. These problems can happen hours, days, or weeks after an injection of JEUVEAU if the muscles that you use to breathe and swallow become weak after the injection. Death can happen as a complication if you have severe problems with swallowing or breathing after treatment with JEUVEAU.
  - People with certain breathing problems may need to use muscles in their neck to help them breathe. These people may be at greater risk for serious breathing problems with JEUVEAU.
  - Swallowing problems may last for several months. People who cannot swallow well may need a feeding tube to receive food and water. If swallowing problems are severe, food or liquids may go into your lungs. People who already have swallowing or breathing problems before receiving JEUVEAU have the highest risk of getting these problems.
- Spread of toxin effects. In some cases, the effect of botulinum toxin may affect areas of the body away from the injection site and cause symptoms of a serious condition called botulism. The symptoms of botulism include:

- loss of strength and muscle weakness all over the body
- blurred vision and drooping eyelids
- trouble saying words clearly
- trouble breathing

- double vision
- hoarseness or change or loss of voice
- loss of bladder control
- trouble swallowing

These symptoms can happen hours, days, or weeks after you receive an injection of JEUVEAU.

These problems could make it unsafe for you to drive a car or do other dangerous activities. See “What should I avoid while receiving JEUVEAU?”

What is JEUVEAU?

JEUVEAU is a prescription medicine that is injected into muscles and used in adults for a short period of time (temporary) to improve the look of moderate to severe frown lines between the eyebrows (glabellar lines).

It is not known if JEUVEAU is safe and effective for use in children.

Do not receive JEUVEAU if you:

- are allergic to JEUVEAU or any of the ingredients in JEUVEAU. See the end of the Medication Guide for a list of ingredients in JEUVEAU.
- had an allergic reaction to any other botulinum toxin product such as rimabotulinumtoxinB (MYOBLOC®), onabotulinumtoxinA (BOTOX®, BOTOX® COSMETIC), abobotulinumtoxinA (DYSPORT®), or incobotulinumtoxinA (XEOMIN®).
- have a skin infection at the planned injection site.

Before receiving JEUVEAU, tell your healthcare provider about all your medical conditions, including if you:

- have a disease that affects your muscles and nerves (such as amyotrophic lateral sclerosis [ALS or Lou Gehrig’s disease], Myasthenia gravis or Lambert-Easton syndrome). See “What is the most important information I should know about JEUVEAU?”
- had any side effect from any botulinum toxin product in the past.
- have or have had a breathing problem, such as asthma or emphysema.
- have or have had swallowing problems.
- have or have had bleeding problems.
- have or have had heart problems.
- have plans to have surgery.
- have weakness of your forehead muscles, such as trouble raising your eyebrows.
- have drooping eyelids.
- have had surgery on your face.
- have had dry eye with use of botulinum toxin products in the past.
- are pregnant or plan to become pregnant. It is not known if JEUVEAU can harm your unborn baby.
- are breastfeeding or plan to breastfeed. It is not known if JEUVEAU passes into breast milk. Talk to your healthcare provider about the best way to feed your baby during treatment with JEUVEAU.

Tell your healthcare provider about all the medicines you take, including prescription and over-the-counter medicines, vitamins and herbal supplements.

Using JEUVEAU with certain other medicines may cause serious side effects. Do not start any new medicines until you have told your healthcare provider that you have received JEUVEAU in the past.

Especially tell your healthcare provider if you:

- have received any other botulinum toxin product in the last 4 months.
- have received injections of botulinum toxin, such as onabotulinumtoxinA (BOTOX®, BOTOX® COSMETIC) rimabotulinumtoxinB (MYOBLOC®), abobotulinumtoxinA (DYSPORT®), or incobotulinumtoxinA (XEOMIN®). Be sure your healthcare provider knows exactly which product you received.

Know the medicines you take. Keep a list of your medicines with you to show your healthcare provider and pharmacist each time you get a new medicine.

How will I receive JEUVEAU?

- JEUVEAU is an injection that your healthcare provider will give you.
- JEUVEAU is injected into your affected muscles.
- JEUVEAU should not be received more than 1 time every 3 months.
- Your healthcare provider may change your dose of JEUVEAU, until you and your healthcare provider find the best dose for you.
- Your healthcare provider will tell you how often you will receive your dose of JEUVEAU injections.

What should I avoid while receiving JEUVEAU?

JEUVEAU may cause loss of strength or general muscle weakness, vision problems, or dizziness within hours to weeks of receiving JEUVEAU. If this happens, do not drive a car, operate machinery, or do other dangerous activities. See “What is the most important information I should know about JEUVEAU?”

What are the possible side effects of JEUVEAU?

JEUVEAU can cause serious side effects, including:

- See “What is the most important information I should know about JEUVEAU?
- Allergic reactions. Symptoms of an allergic reaction to JEUVEAU may include: itching, rash, hives, wheezing, trouble breathing, or you may become dizzy or faint. Tell your healthcare provider or get emergency medical help right away if you develop wheezing or trouble breathing, or if you feel dizzy or faint.
- Heart problems. Irregular heartbeat and heart attack that have caused death have happened in some people who received botulinum toxin products.
- Eye problems. Dry eye, reduced blinking, and corneal problems have happened in some people who receive JEUVEAU to treat glabellar lines. Tell your healthcare provider if you develop eye pain or irritation, sensitivity to light, or changes in your vision.

The most common side effects of JEUVEAU include:

- headache
- eyelid drooping
- upper respiratory infection
- increased white blood cell count in your blood

These are not all the possible side effect of JEUVEAU.

Call your doctor for medical advice about side effects. You may report side effects to FDA at 1-800-FDA-1088.

General information about the safe and effective use of JEUVEAU.

Medicines are sometime prescribed for purposes other than those listed in a Medication Guide. You can ask your healthcare provider or pharmacist for information about JEUVEAU that is written for healthcare professionals.

What are the ingredients in JEUVEAU?

Active ingredient: botulinum toxin type A

Inactive ingredients: human serum albumin and sodium chloride

Manufactured by: Evolus Inc., 520 Newport Center Drive, Suite 1200, Newport Beach, CA 92660

US License No. 2070

©2023 Evolus Inc. All rights reserved. All trademarks are the property of their respective owners.

This Medication Guide has been approved by the U.S. Food and Drug Administration.

Issued: 04 2023

PRINCIPAL DISPLAY PANEL - Carton Label

Carton Label

Principal Panel

prabotulinumtoxinA-xvfs

Jeuveau®
for Injection

100 UNITS/VIAL

For Intramuscular Use
1 Single-Dose Vial

ATTENTION: Dispense the enclosed
Medication Guide to each patient

Designed by Evolus

Left Panel

WARNING: Dosing units of botulinum
toxins are not interchangeable
between commercial products.

Store unopened vial refrigerated
at 2°C to 8°C (36°F to 46°F) in the
original carton to protect from light.
DO NOT FREEZE.
Each vial of Jeuveau
(prabotulinumtoxinA-xvfs)
contains 100 Units of
botulinum toxin type A
neurotoxin complex, human
serum albumin (0.5 mg), and
sodium chloride (0.9 mg).

No U.S. standard of potency.

Vacuum-dried.

Contains no preservative.

Rx only

Manufactured by: Evolus, Inc.
Newport Beach, CA
US License No. 2070

at: Daewoong Pharmaceuticals
Seoul, Korea

www.jeuveau.com
NDC 72301-595-10

Made in Korea

Right Panel

Single-Dose Vial. Discard unused
portion.

Only reconstitute each vial with
sterile, preservative-free 0.9%
Sodium Chloride Injection, USP by
slowly injecting diluent and gently
rotating the vial. Store unused
reconstituted JEUVEAU
refrigerated between 2° to 8°C
(36°F to 46°F) in the original carton
to protect from light for up to
24 hours until time of use. Do not
freeze reconstituted JEUVEAU.
Discard 24 hours after reconstitution.

Dosage and Dilution: See
Prescribing Information.